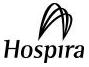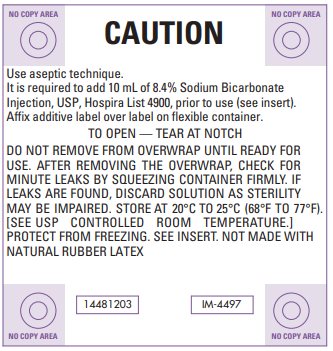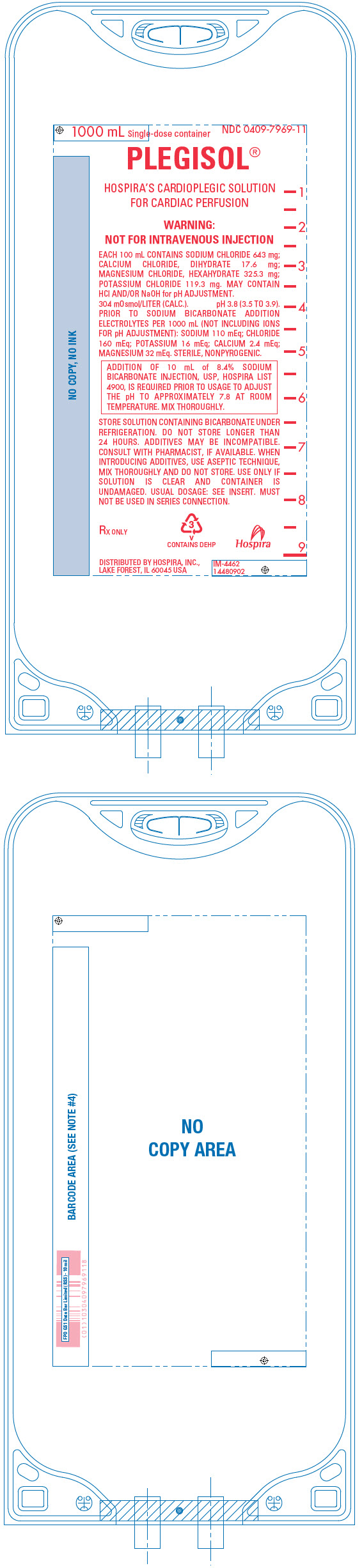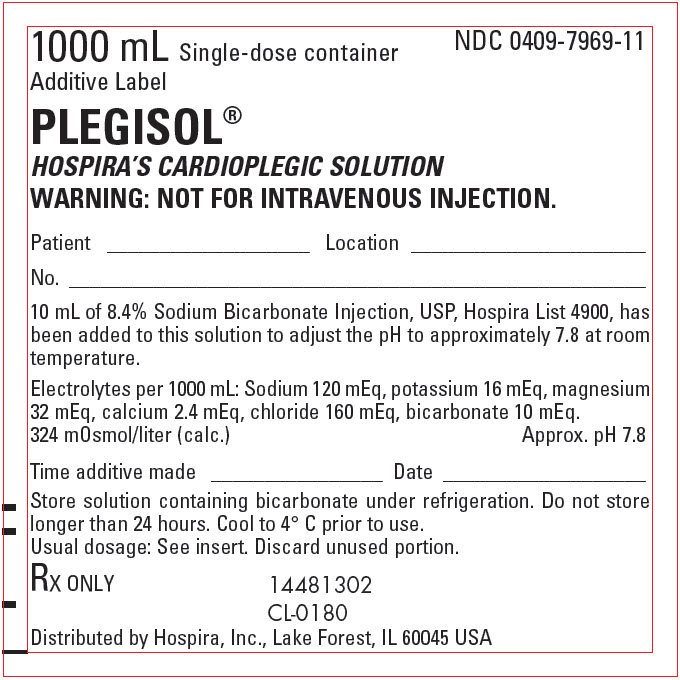 DRUG LABEL: Plegisol
NDC: 0409-7969 | Form: INJECTION, SOLUTION
Manufacturer: Hospira, Inc.
Category: prescription | Type: HUMAN PRESCRIPTION DRUG LABEL
Date: 20240318

ACTIVE INGREDIENTS: POTASSIUM CHLORIDE 119.3 mg/100 mL; SODIUM CHLORIDE 643 mg/100 mL; CALCIUM CHLORIDE 17.6 mg/100 mL; MAGNESIUM CHLORIDE 325.3 mg/100 mL
INACTIVE INGREDIENTS: HYDROCHLORIC ACID; SODIUM HYDROXIDE; WATER

PLEGISOL®

CARDIOPLEGIC SOLUTION FOR CARDIAC PERFUSION

NOT FOR INTRAVENOUS INJECTION

Flexible Plastic Container

Rx Only

DESCRIPTION

Plegisol (Cardioplegic Solution) is a sterile, nonpyrogenic, essentially isotonic, formulation of electrolytes in water for injection. It is a "core solution" intended for use only after addition of sodium bicarbonate to adjust pH prior to administration. After buffering with sodium bicarbonate it is suitable for cardiac instillation (usually with hypothermia) to induce arrest during open heart surgery. Other agents may be added to the solution prior to instillation (See INSTRUCTIONS FOR USE).

Each 100 mL of solution contains calcium chloride, dihydrate 17.6 mg, magnesium chloride, hexahydrate 325.3 mg, potassium chloride 119.3 mg and sodium chloride 643 mg in water for injection. May contain HCl or NaOH for pH adjustment. Electrolyte content per liter (not including ions for pH adjustment): Calcium (Ca^++) 2.4 mEq; magnesium (Mg^++) 32 mEq; potassium (K^+) 16 mEq; sodium (Na^+) 110 mEq; chloride (Cl‾) 160 mEq. Osmolar concentration, 304 mOsmol/liter (calc.); pH 3.8 (3.5 to 3.9) prior to sodium bicarbonate addition.

It is required that 10 mL (840 mg) of 8.4% Sodium Bicarbonate Injection, USP (10 mEq each of sodium and bicarbonate) be added aseptically and thoroughly mixed with each 1000 mL of cardioplegic solution to adjust pH. Use 10 mL of Hospira List 4900, 8.4% Sodium Bicarbonate Injection, USP, to achieve the approximate pH of 7.8 when measured at room temperature. Use of any other Sodium Bicarbonate Injection may not achieve this pH due to the varying pH's of Sodium Bicarbonate Injections. Due to its inherent instability with other components, sodium bicarbonate must be added just prior to administration. After this addition, the solution must be stored under refrigeration and be used within 24 hours.

The buffered admixture contains the following electrolytes (per liter): Ca^++ 2.4 mEq, Mg^++ 32 mEq, K^+ 16 mEq, Na^+ 120 mEq, Cl‾ 160 mEq and bicarbonate (HCO3‾) 10 mEq; osmolar concentration, 324 mOsmol/liter (calc.); pH 7.8 (approx.). If other agents are added, these values may be altered.

The solution contains no bacteriostat, or antimicrobial agent and is intended only for use (after adjusting pH with sodium bicarbonate) in a single operative procedure. When smaller amounts are required, the unused portion should be discarded.

Plegisol with added sodium bicarbonate used as a coronary artery infusate induces cardiac arrest, combats ischemic ionic disturbances, buffers ischemic acidosis and protects energy sources for functional recovery after ischemia.

Calcium Chloride, USP is chemically designated calcium chloride, dihydrate (CaCl2 • 2 H2O), white fragments or granules freely soluble in water.

Magnesium Chloride, USP is chemically designated magnesium chloride, hexahydrate (MgCl2 • 6 H2O), deliquescent flakes or crystals very soluble in water.

Potassium Chloride, USP is chemically designated KCl, a white granular powder freely soluble in water.

Sodium Chloride, USP is chemically designated NaCl, a white crystalline powder freely soluble in water.

Water for Injection, USP is chemically designated H2O.

The flexible plastic container is fabricated from a specially formulated polyvinyl chloride. Water can permeate from inside the container into the overwrap but not in amounts sufficient to affect the solution significantly. Solutions in contact with the plastic container may leach out certain chemical components from the plastic in very small amounts; however, biological testing was supportive of the safety of the plastic container materials. Exposure to temperatures above 25°C/77°F during transport and storage will lead to minor losses in moisture content. Higher temperatures lead to greater losses. It is unlikely that these minor losses will lead to clinically significant changes within the expiration period.

CLINICAL PHARMACOLOGY

Plegisol with added sodium bicarbonate when cooled and instilled into the coronary artery vasculature, causes prompt arrest of cardiac electromechanical activity, combats intracellular ion losses and buffers ischemic acidosis. When used with hypothermia and ischemia, the action may be characterized as cold ischemic potassium-induced cardioplegia. This is conducive to providing the surgeon with a quiet, relaxed heart and bloodless field of operation.

Calcium (Ca^++) ion in low concentration is included in the solution to maintain integrity of cell membrane to ensure that there is no likelihood of calcium paradox during reperfusion.

Magnesium (Mg^++) ion may help stabilize the myocardial membrane by inhibiting a myosin phosphorylase, which protects adenosine triphosphate (ATP) reserves for postischemic activity. The protective effects of magnesium and potassium have been shown to be additive.

Potassium (K^+) ion concentration is responsible for prompt cessation of mechanical myocardial contractile activity. The immediacy of the arrest thus preserves energy supplies for postischemic contractile activity in diastole.

The chloride (Cl‾) and sodium (Na^+) ions have no specific role in the production of cardiac arrest. Sodium is essential to maintain ionic integrity of myocardial tissue. The chloride ions are present to maintain the electroneutrality of the solution.

Added bicarbonate (HCO3‾) anion is included as a buffer to render the solution slightly alkaline and compensate for the metabolic acidosis that accompanies ischemia.

Extemporaneous alternative buffering to the described formulation of this solution is not recommended.

INDICATIONS AND USAGE

Plegisol (Cardioplegic Solution) when suitably buffered in combination with ischemia and hypothermia is used to induce cardiac arrest during open heart surgery.

CONTRAINDICATIONS

Plegisol must not be administered without the addition of 8.4% Sodium Bicarbonate Injection, USP, Hospira List 4900.

NOT FOR INTRAVENOUS INJECTION.

This solution is only for instillation into cardiac vasculature after buffering with sodium bicarbonate.

WARNINGS

This solution should be used only by those trained to perform open heart surgery. This solution is intended only for use during cardiopulmonary bypass when the coronary circulation is isolated from the systemic circulation (See INDICATIONS AND USAGE).

Do not instill the solution into the coronary vasculature unless sodium bicarbonate has been added. If large volumes of cardioplegic solution are infused and allowed to return to the heart lung machine without any venting from the right heart, then plasma magnesium and potassium levels may rise. Development of severe hypotension and metabolic acidosis while on bypass has been reported when large volumes (8 to 10 liters) of solution are instilled and allowed to enter the pump and then the systemic circulation. Right heart venting is therefore recommended. The buffered solution with added sodium bicarbonate should be cooled to 4°C prior to administration and used within 24 hours of mixing.

PRECAUTIONS

Myocardial temperature should be monitored during surgery to maintain hypothermia.

Continuous electrocardiogram monitoring is essential to detect changes in myocardial activity during the procedure.

Appropriate equipment to defibrillate the heart following cardioplegia should be readily available.

Inotropic support drugs should be available during postoperative recovery.

Do not administer unless solution is clear and container is undamaged. Discard unused portion.

Drug Interactions

Additives may be incompatible. Consult with pharmacist, if available. When introducing additives, use aseptic technique, mix thoroughly and do not store (See INSTRUCTIONS FOR USE).

PREGNANCY

Pregnancy: Animal reproduction studies have not been conducted with Plegisol. It is also not known whether this solution can cause fetal harm when administered to a pregnant woman or can affect reproduction capacity. Plegisol should be given to a pregnant woman only if clearly needed.

Pediatric Use

Safety and effectiveness in pediatric patients have not been established. Because of differences in structure, function, and metabolism, clinical myocardial protection strategies and Cardioplegia solutions that are effective in adult hearts may be less effective in the immature heart.

Geriatric Use

Clinical studies of Plegisol did not include sufficient numbers of subjects aged 65 and over to determine whether they responded differently from younger subjects. Other reported clinical experience has not identified differences in responses between older and younger patients.

In general, dose selection for an elderly patient should be cautious, usually starting at the low end of the dosage range reflecting the greater frequency of decreased hepatic, renal, or cardiac function, and of concomitant disease.

This product is unique in that there is no hepatic or renal excretion and specific adjustments for dosing in the elderly are not known.

ADVERSE REACTIONS

Intraoperative and perioperative potential hazards of open heart surgery include myocardial infarction, electrocardiographic abnormalities, and arrhythmias, including ventricular fibrillation. Spontaneous recovery after cardioplegic cardiac arrest may be delayed or absent when circulation is restored. Defibrillation by electric shock may be required to restore normal cardiac function.

OVERDOSAGE

Overzealous instillation of the solution may result in unnecessary dilatation of the myocardial vasculature and leakage into the perivascular myocardium, possibly causing tissue edema (See WARNINGS, PRECAUTIONS, and ADVERSE REACTIONS).

DOSAGE AND ADMINISTRATION

The following information is suggested as a guide and is subject to variation according to the preference and experience of the surgeon.

It is required that 10 mL (840 mg) of 8.4% Sodium Bicarbonate Injection, USP (10 mEq each of sodium and bicarbonate) be added aseptically and thoroughly mixed with each 1000 mL of cardioplegic solution to adjust pH. Use 10 mL of Hospira List 4900, 8.4% Sodium Bicarbonate Injection, USP, to achieve the approximate pH of 7.8 when measured at room temperature. Use of any other Sodium Bicarbonate Injection may not achieve this pH due to the varying pH's of Sodium Bicarbonate Injections. Due to its inherent instability with other components, sodium bicarbonate must be added just prior to administration. After this addition, the solution must be used within 24 hours. The solution should be cooled to 4°C prior to use.

Following institution of cardiopulmonary bypass at perfusate temperatures of 28° to 30°C, and after cross-clamping of the ascending aorta, the buffered solution is administered by rapid infusion into the aortic root. The initial rate of infusion may be 300 mL/m^2/minute (about 540 mL/min in a 5'8", 70 kg adult with 1.8 square meters of surface area) given for a period of two to four minutes. Concurrent external cooling (regional hypothermia of the pericardium) may be accomplished by instilling a refrigerated (4°C) physiologic solution such as Normosol®-R (balanced electrolyte replacement solution) or Ringer's Injection, USP into the chest cavity.

Should myocardial electromechanical activity persist or recur, the solution may be reinfused at a rate of 300 mL/m^2/min for a period of two minutes. Reinfusion of the solution may be repeated every 20 to 30 minutes or sooner if myocardial temperature rises above 15° to 20°C or returning cardiac activity is observed. The regional hypothermia solution around the heart also may be replenished continuously or periodically in order to maintain adequate hypothermia. Suction may be used to remove warmed infusates. An implanted thermistor probe may be used to monitor myocardial temperature.

The volumes of solution instilled into the aortic root may vary depending on the duration or type of open heart surgical procedure.

Parenteral drug products should be inspected visually for particulate matter and discoloration prior to administration, whenever solution and container permit (See PRECAUTIONS).

INSTRUCTIONS FOR USE

To Open

Tear outer wrap at notch and remove solution container. If supplemental medication is desired, follow directions below before preparing for administration. Some opacity of the plastic due to moisture absorption during the sterilization process may be observed. This is normal and does not affect the solution quality or safety. The opacity will diminish gradually.

To add 10 mL of 8.4% Sodium Bicarbonate Injection, USP, Hospira List 4900, and other supplemental medication, follow directions below before preparing for administration.

To Add Medication

Prepare additive port.
Using aseptic technique and an additive delivery needle of appropriate length, puncture resealable additive port at target area, inner diaphragm and inject. Withdraw needle after injecting medication.
The additive port may be protected by covering with an additive cap.
Mix container contents thoroughly.

Preparation for Administration

(Use aseptic technique)

Close flow control clamp of administration set.
Remove cover from outlet port at bottom of container.
Insert piercing pin of administration set into port with a twisting motion until the set is firmly seated. NOTE: See full directions on administration set carton.
Suspend container from hanger.
Squeeze and release drip chamber to establish proper fluid level in chamber.
Attach aortic infusion device to set.
Open flow control clamp to expel air from set and aortic infusion device. Close clamp.
Position aortic infusion device to introduce solution into aortic root.
Regulate rate of administration with flow control clamp.

HOW SUPPLIED

Plegisol® (Cardioplegic Solution) is supplied (without sodium bicarbonate) as follows:

Unit of Sale

NDC 0409-7969-05

Case of 12 single-dose 1000 mL flexible plastic containers

WARNING: Do not use flexible container in series connections.

Store at 20°C to 25°C (68°F to 77°F). [See USP Controlled Room Temperature.] Protect from freezing.

Distributed by Hospira, Inc., Lake Forest, IL 60045 USA

LAB-1244-3.0

Revised: 01/2021

PRINCIPAL DISPLAY PANEL - 1000 mL Overwrap Label

CAUTION

Use aseptic technique.
It is required to add 10 mL of 8.4% Sodium Bicarbonate
Injection, USP, Hospira List 4900, prior to use (see insert).
Affix additive label over label on flexible container.

TO OPEN — TEAR AT NOTCH

DO NOT REMOVE FROM OVERWRAP UNTIL READY FOR
USE. AFTER REMOVING THE OVERWRAP, CHECK FOR
MINUTE LEAKS BY SQUEEZING CONTAINER FIRMLY. IF
LEAKS ARE FOUND, DISCARD SOLUTION AS STERILITY
MAY BE IMPAIRED. STORE AT 20°C TO 25°C (68°F TO 77°F).
[SEE USP CONTROLLED ROOM TEMPERATURE.]
PROTECT FROM FREEZING. SEE INSERT. NOT MADE WITH
NATURAL RUBBER LATEX

14481203
IM-4497

PRINCIPAL DISPLAY PANEL - 1000 mL Bag

1000 mL Single-dose container
NDC 0409-7969-11

PLEGISOL®

HOSPIRA'S CARDIOPLEGIC SOLUTION
FOR CARDIAC PERFUSION

WARNING:
NOT FOR INTRAVENOUS INJECTION

EACH 100 mL CONTAINS SODIUM CHLORIDE 643 mg;
CALCIUM CHLORIDE, DIHYDRATE 17.6 mg;
MAGNESIUM CHLORIDE, HEXAHYDRATE 325.3 mg;
POTASSIUM CHLORIDE 119.3 mg. MAY CONTAIN
HCl AND/OR NaOH for pH ADJUSTMENT.
304 mOsmol/LITER (CALC.). pH 3.8 (3.5 TO 3.9).

PRIOR TO SODIUM BICARBONATE ADDITION
ELECTROLYTES PER 1000 mL (NOT INCLUDING IONS
FOR pH ADJUSTMENT): SODIUM 110 mEq; CHLORIDE
160 mEq; POTASSIUM 16 mEq; CALCIUM 2.4 mEq;
MAGNESIUM 32 mEq. STERILE, NONPYROGENIC.

ADDITION OF 10 mL of 8.4% SODIUM
BICARBONATE INJECTION, USP, HOSPIRA LIST
4900, IS REQUIRED PRIOR TO USAGE TO ADJUST
THE pH TO APPROXIMATELY 7.8 AT ROOM
TEMPERATURE. MIX THOROUGHLY.

STORE SOLUTION CONTAINING BICARBONATE UNDER
REFRIGERATION. DO NOT STORE LONGER THAN
24 HOURS. ADDITIVES MAY BE INCOMPATIBLE.
CONSULT WITH PHARMACIST, IF AVAILABLE. WHEN
INTRODUCING ADDITIVES, USE ASEPTIC TECHNIQUE,
MIX THOROUGHLY AND DO NOT STORE. USE ONLY IF
SOLUTION IS CLEAR AND CONTAINER IS
UNDAMAGED. USUAL DOSAGE: SEE INSERT. MUST
NOT BE USED IN SERIES CONNECTION.

RX ONLY
3
v
CONTAINS DEHP
Hospira

DISTRIBUTED BY HOSPIRA, INC.,
LAKE FOREST, IL 60045 USA

IM-4462
14480902

PRINCIPAL DISPLAY PANEL - 1000 mL Bag Additive Label

1000 mL Single-dose container
Additive Label

NDC 0409-7969-11

PLEGISOL®
HOSPIRA'S CARDIOPLEGIC SOLUTION
WARNING: NOT FOR INTRAVENOUS INJECTION.

Patient _________________ Location ________________

No. ____________________________________________

10 mL of 8.4% Sodium Bicarbonate Injection, USP, Hospira List 4900, has
been added to this solution to adjust the pH to approximately 7.8 at room
temperature.

Electrolytes per 1000 mL: Sodium 120 mEq, potassium 16 mEq, magnesium
32 mEq, calcium 2.4 mEq, chloride 160 mEq, bicarbonate 10 mEq.

324 mOsmol/liter (calc.)
Approx. pH 7.8

Time additive made ______________ Date _____________

Store solution containing bicarbonate under refrigeration. Do not store
longer than 24 hours. Cool to 4° C prior to use.
Usual dosage: See insert. Discard unused portion.

RX ONLY

14481302
CL-0180

Distributed by Hospira, Inc., Lake Forest, IL 60045 USA